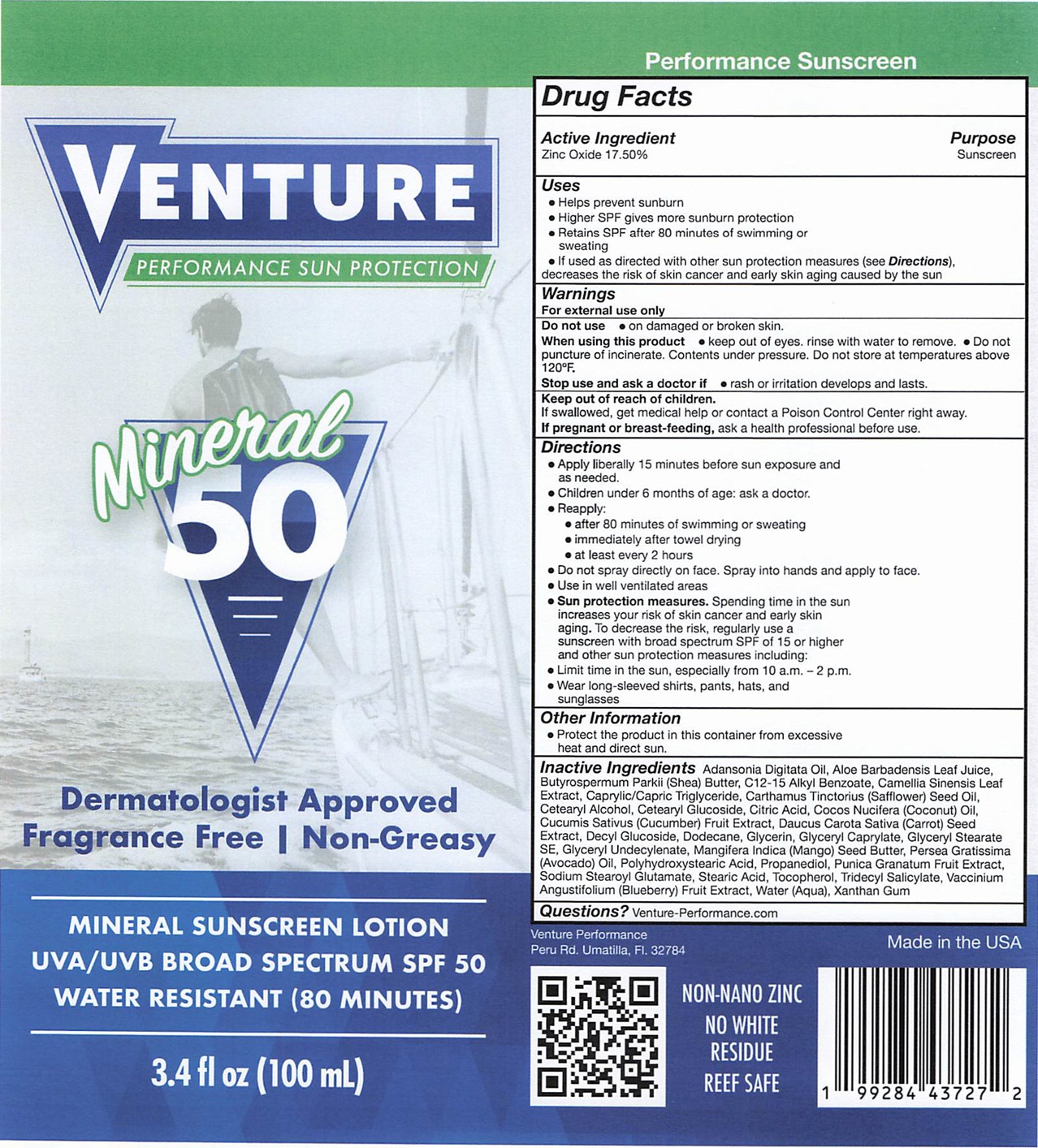 DRUG LABEL: Venture Performance Sun Protection Mineral Sunscreen SPF 50
NDC: 87241-911 | Form: LOTION
Manufacturer: Venture Performance Inc
Category: otc | Type: HUMAN OTC DRUG LABEL
Date: 20251201

ACTIVE INGREDIENTS: ZINC OXIDE 175 mg/1 mL
INACTIVE INGREDIENTS: ADANSONIA DIGITATA SEED OIL; ALOE VERA LEAF JUICE; SHEA BUTTER; ALKYL (C12-15) BENZOATE; GREEN TEA LEAF; MEDIUM-CHAIN TRIGLYCERIDES; SAFFLOWER OIL; CETOSTEARYL ALCOHOL; CETEARYL GLUCOSIDE; CITRIC ACID MONOHYDRATE; COCONUT OIL; CUCUMBER; DAUCUS CAROTA SUBSP. SATIVUS SEED; DODECANE; GLYCERIN; GLYCERYL MONOCAPRYLATE; GLYCERYL STEARATE SE; MANGIFERA INDICA SEED BUTTER; AVOCADO; PROPANEDIOL; POMEGRANATE; SODIUM STEAROYL GLUTAMATE; STEARIC ACID; TOCOPHEROL; TRIDECYL SALICYLATE; BLUEBERRY; WATER; XANTHAN GUM

Venture Performance Sun Protection Mineral Sunscreen SPF 50

Active Ingredient

Zinc Oxide 17.50%

Purpose

Sunscreen

Uses

● Helps prevent sunburn
● Higher SPF gives more sunburn protection
● Retains SPF after 80 minutes of swimming or sweating
● If used as directed with other sun protection measures (see Directions), decreases the risk of skin cancer and early skin aging caused by the sun

Warnings

For external use only

Do not use

● on damaged or broken skin.

When using this product

● keep out of eyes, rinse with water to remove.

● Do not puncture of incinerate. Contents under pressure. Do not store at temperatures above 120°F.

Stop use and ask a doctor if

● rash or irritation develops and lasts.

Keep out of reach of children.

If swallowed, get medical help or contact a Poison Control Center right away.

If pregnant or breast-feeding,

ask a health professional before use.

Directions

●Apply liberally 15 minutes before sun exposure and as needed.
● Children under 6 months of age: ask a doctor.
● Reapply:
● after 80 minutes of swimming or sweating
● immediately after towel drying
● at least every 2 hours
● Do not spray directly on face. Spray into hands and apply to face.
● Use in well ventilated areas
● Sun protection measures.Spending time In the sun increases your risk of skin cancer and early skin aging. To decrease the risk, regularly use a sunscreen with broad spectrum SPF of 15 or higher and other sun protection measures including:
● Limit time in the sun. especially from 10 a.m. -2 p.m.
● Wear long-sleeved shirts, pants, hats, and sunglasses

Other Information

● Protect the product in this container from excessive heat and direct sun.

Inactive Ingredients

Adansonia Digitata Oil, Aloe Barbadensis Leaf Juice, Butyrospermum Parkii (Shea) Butter, C12-15 Alkyl Benzoate, Camellia Sinensis Leaf Extract, Caprylic/Capric Triglyceride, Carthamus Tinctorius (Safflower) Seed Oil, Cetearyl Alcohol. Cetearyl Glucoside, Citric Acid, Cocos Nucifera (Coconut) Oil. Cucumis Sativus (Cucumber) Fruit Extract. Daucus Carota Sativa (Carrot) Seed Extract, Decyi Glucoside, Dodecane, Glycerin, Glyceryl Caprylate, Glyceryl Stearate SE, Glyceryl Undecylenate, Mangifera Indica (Mango) Seed Butter, Persea Gratissima (Avocado) on. Polyhydroxystearic Acid, Propanediol, Punica Granatum Fruit Extract, Sodium Stearoyl Glutamate, Stearic Acid. Tocopherol, Tridecyl Salicylate, Vaccinium Angustifolium (Blueberry) Fruit Extract, Water (Aqua), Xanthan Gum

Questions?

Venture-Performance.com